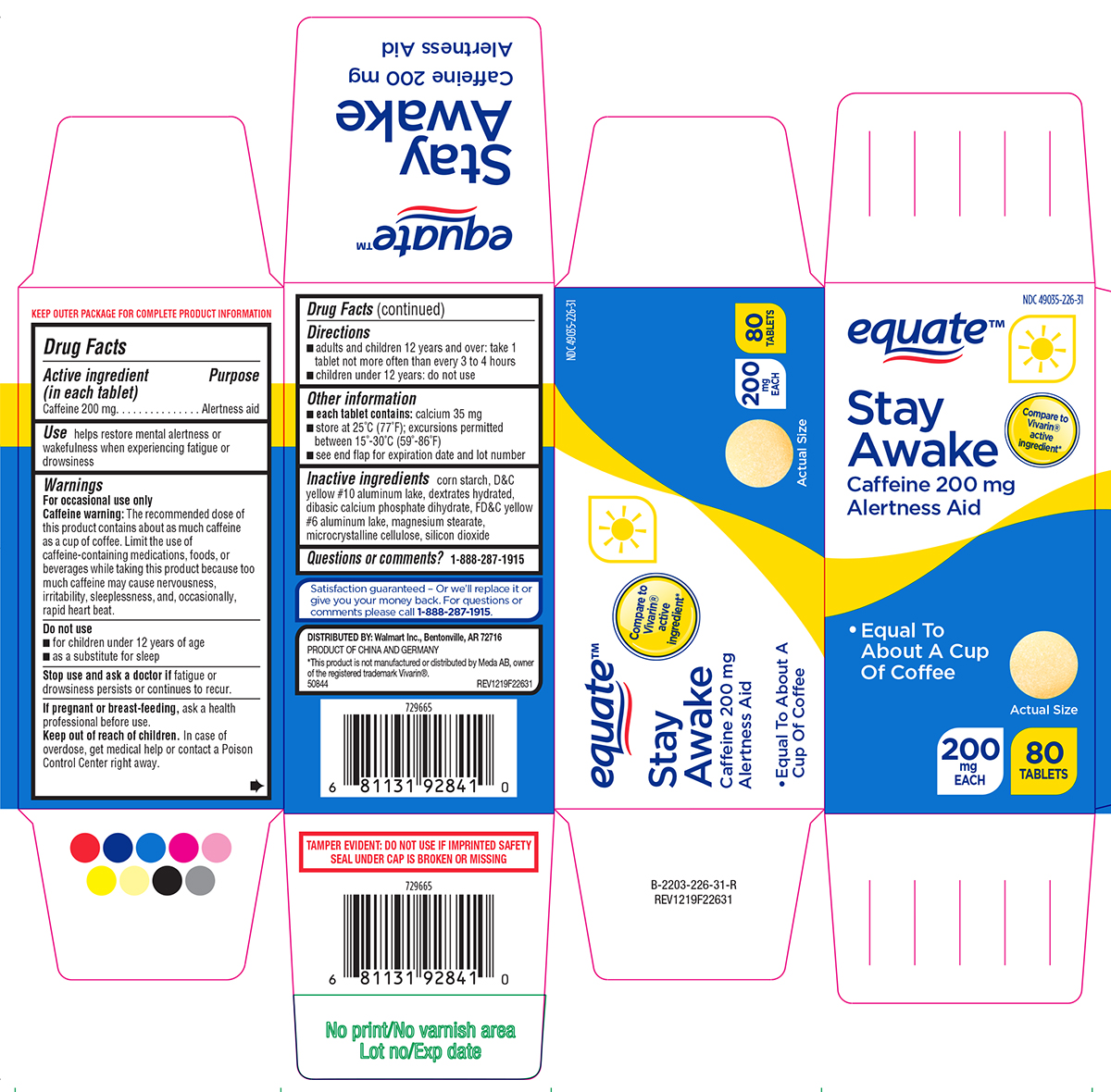 DRUG LABEL: Stay Awake
NDC: 49035-226 | Form: TABLET
Manufacturer: Wal-Mart Stores Inc
Category: otc | Type: HUMAN OTC DRUG LABEL
Date: 20250607

ACTIVE INGREDIENTS: CAFFEINE 200 mg/1 1
INACTIVE INGREDIENTS: STARCH, CORN; D&C YELLOW NO. 10 ALUMINUM LAKE; DEXTROSE MONOHYDRATE; DIBASIC CALCIUM PHOSPHATE DIHYDRATE; FD&C YELLOW NO. 6 ALUMINUM LAKE; MAGNESIUM STEARATE; MICROCRYSTALLINE CELLULOSE; SILICON DIOXIDE

Equate 44-226

Active ingredient (in each tablet)

Caffeine 200 mg

Purpose

Alertness aid

Use

helps restore mental alertness or wakefulness when experiencing fatigue or drowsiness

Warnings

For occasional use only

Caffeine warning: The recommended dose of this product contains about as much caffeine as a cup of coffee. Limit the use of caffeine-containing medications, foods, or beverages while taking this product because too much caffeine may cause nervousness, irritability, sleeplessness, and, occasionally, rapid heart beat.

Do not use

- for children under 12 years of age
- as a substitute for sleep

Stop use and ask a doctor if

fatigue or drowsiness persists or continues to recur.

If pregnant or breast-feeding,

ask a health professional before use.

Keep out of reach of children.

In case of overdose, get medical help or contact a Poison Control Center right away.

Directions

- adults and children 12 years and over: take 1 tablet not more often than every 3 to 4 hours
- children under 12 years: do not use

Other information

- each tablet contains: calcium 35 mg
- store at 25ºC (77ºF); excursions permitted between 15º-30ºC (59º-86ºF)
- see end flap for expiration date and lot number

Inactive ingredients

corn starch, D&C yellow #10 aluminum lake, dextrates hydrated, dibasic calcium phosphate dihydrate, FD&C yellow #6 aluminum lake, magnesium stearate, microcrystalline cellulose, silicon dioxide

Questions or comments?

1-888-287-1915

Principal Display Panel

equate™

NDC 49035-226-31

Compare to
Vivarin®
active
ingredient*

Stay Awake
Caffeine 200 mg
Alertness Aid

• Equal To About A
Cup Of Coffee

200
mg
EACH

80
TABLETS

Actual Size

TAMPER EVIDENT: DO NOT USE IF IMPRINTED SAFETY
SEAL UNDER CAP IS BROKEN OR MISSING

Satisfaction guaranteed - Or we'll replace it or
give you your money back. For questions or
comments please call 1-888-287-1915.

DISTRIBUTED BY: Walmart Inc., Bentonville, AR 72716
PRODUCT OF CHINA AND GERMANY

*This product is not manufactured or distributed by Meda AB, owner
of the registered trademark Vivarin®.
50844 REV1219F22631

Equate 44-226